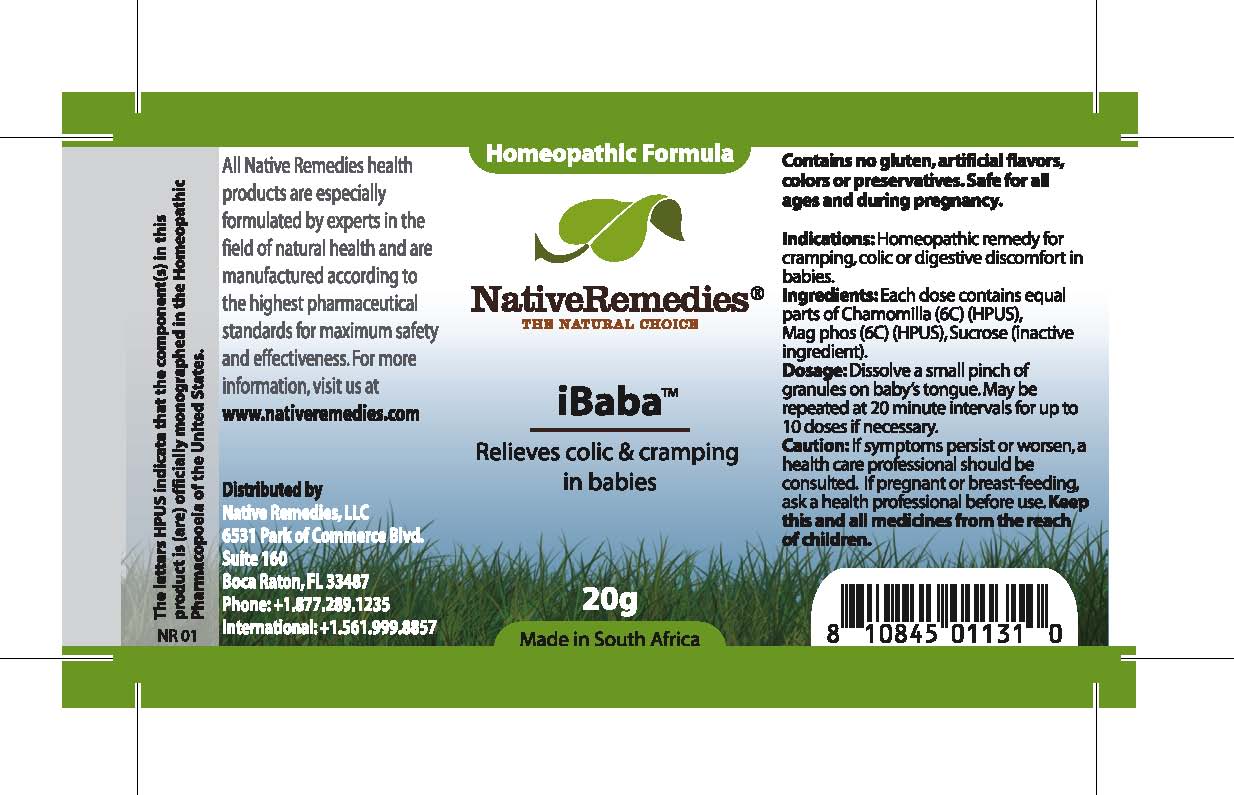 DRUG LABEL: iBaba
NDC: 68647-103 | Form: GRANULE
Manufacturer: Feelgood Health
Category: homeopathic | Type: HUMAN OTC DRUG LABEL
Date: 20100802

ACTIVE INGREDIENTS: MATRICARIA RECUTITA 6 [hp_C]/100 mg; MAGNESIUM PHOSPHATE 6 [hp_C]/100 mg
INACTIVE INGREDIENTS: SUCROSE 20000 mg/20000 mg

IBABA

PURPOSE

Relieves colic and cramping in babies

INDICATIONS AND USAGE

Indications: Homeopathic remedy for cramping, colic or digestive discomfort in babies.

DOSAGE AND ADMINISTRATION

Dosage: Dissolve a small pinch of granules on baby’s tongue. May be repeated at 20 minute intervals for up to 10 doses if necessary.

GENERAL PRECAUTIONS

Caution: If symptoms persist or worsen, a health care professional should be consulted.

ACTIVE INGREDIENT

Ingredients: Each dose contains equal parts of Chamomilla (6C) (HPUS), Mag phos (6C) (HPUS)

Sucrose (inactive ingredient).

PREGNANCY

If pregnant or breastfeeding, ask a health professional before use.

WARNINGS

Contains no gluten, artificial flavors, colors or preservatives. Safe for all ages and during pregnancy.

PATIENT COUNSELING INFORMATION

All Native Remedies health products are especially formulated by experts in the field of natural health and are manufactured according to the highest pharmaceutical standards for maximum safety and effectiveness. For more information, visit us at www.nativeremedies.com

Distributed by

Native Remedies, LLC

6531 Park of Commerce Blvd.

Suite 160

Boca Raton, FL 33487

Phone: 1.877.289.1235

International: + 1.561.999.8857

The letters HPUS indicate that the component(s) in this product is (are) officially monographed in the Homeopathic Pharmacopoeia of the United States.

KEEP OUT OF REACH OF CHILDREN

Keep this and all medicines from the reach of children.